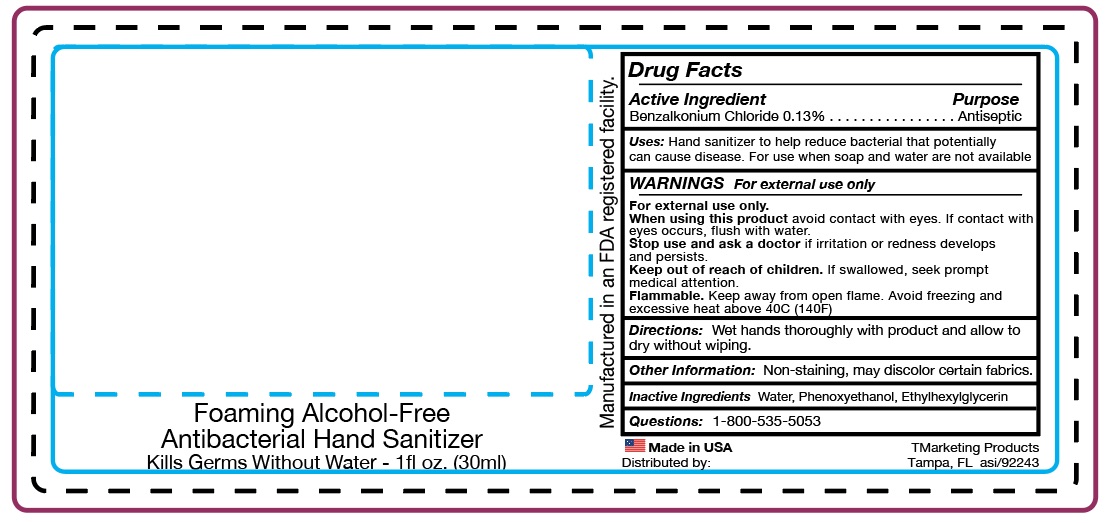 DRUG LABEL: BZK Hand Sanitizer
NDC: 58418-187 | Form: SPRAY
Manufacturer: Tropical Enterprises International, Inc.
Category: otc | Type: HUMAN OTC DRUG LABEL
Date: 20200414

ACTIVE INGREDIENTS: BENZALKONIUM CHLORIDE 0.039 g/30 mL
INACTIVE INGREDIENTS: ETHYLHEXYLGLYCERIN; WATER; PHENOXYETHANOL

BK-S/F-0312012-CRC
BZK non-alcohol sanitizer

ACTIVE INGREDIENT

Benzalkonium Chloride 0.13%

Purpose..... Antiseptic

INDICATIONS AND USAGE

Use Hand Sanitizer to help reduce bacteria that potentially can cause disease.

For use when soap and water are not available.

RECENT MAJOR CHANGES

Use Hand Sanitizer to help reduce bacteria that potentially can cause disease.

For use when soap and water are not available.

DOSAGE AND ADMINISTRATION

Directions: Wet hands thoroughly with product and allow to dry without wiping.

INACTIVE INGREDIENT

Inactive Ingredients Water, Phenoxyethanol, Ethylhexylglycerin

WARNING

WARNINGS: For external use only.

When using this product avoid contact with eyes.

If contact with eyes occurs, flush with water.

Stop use and ask a doctor if irritation or redness develops and perists.

Stop use and ask a doctor if irritation or redness

develops and persists.

Keep out of reach of children. If swallowed, seek prompt medical attention.

SAFE HANDLING WARNING

Flammable. Keep away from open flames.

Avoid freezing and excessive heat above 40C (104F)

Questions: 1-800-535-5053

Other Information: Non-staining, may discolor certain fabrics.